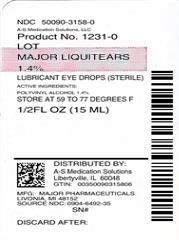 DRUG LABEL: Major LiquiTears
NDC: 50090-3158 | Form: SOLUTION/ DROPS
Manufacturer: A-S Medication Solutions
Category: otc | Type: HUMAN OTC DRUG LABEL
Date: 20200118

ACTIVE INGREDIENTS: POLYVINYL ALCOHOL 14 mg/1 mL
INACTIVE INGREDIENTS: BENZALKONIUM CHLORIDE; SODIUM PHOSPHATE, DIBASIC, MONOHYDRATE; EDETATE DISODIUM; SODIUM PHOSPHATE, MONOBASIC, DIHYDRATE; WATER; SODIUM CHLORIDE

Active ingredient Purpose

Polyvinyl Alcohol 1.4%..................................... Lubricant

Uses

- to prevent further irritation
- to relieve dryness of the eye

Warnings

Do not use

- if solution changes color or becomes cloudy

When using this product

- do not touch tip of container to any surface to avoid contamination
- replace cap after each use

Stop use and ask a doctor if

- you experience eye pain, changes in vision, continued redness or irritation of the eye
- condition worsens or persists for more than 72 hours

Keep out of reach of children. If swallowed, get medical help or contact a Poison Control Center right away.

Directions

- instill 1 to 2 drops in the affected eye(s) as needed

Other information

- store at 15°-25°C (59°-77°F)
- keep tightly closed

Inactive ingredients

benzalkonium chloride, dibasic sodium phosphate hydrate, edetate disodium hydrate, monobasic sodium phosphate dihydrate, purified water, sodium chloride

DOSAGE AND ADMINISTRATION

Distributed by:

Major Pharmaceuticals

31778 Enterprise Drive

Livonia, MI 48150 USA

Made in Korea

HOW SUPPLIED

Product: 50090-3158

NDC: 50090-3158-0 15 mL in a BOTTLE, DROPPER / 1 in a CARTON